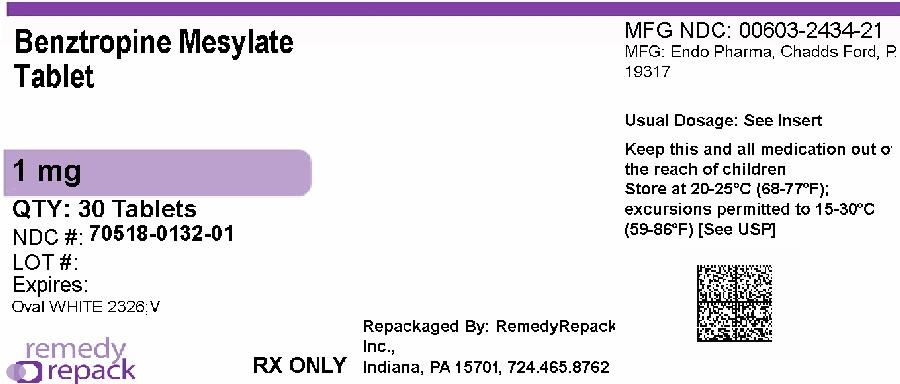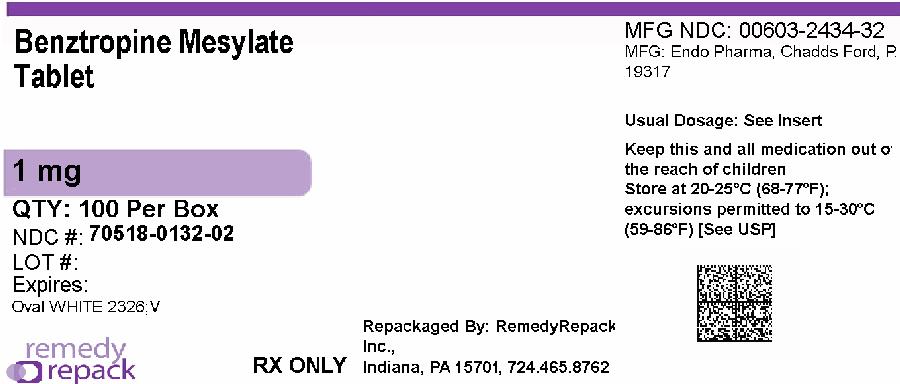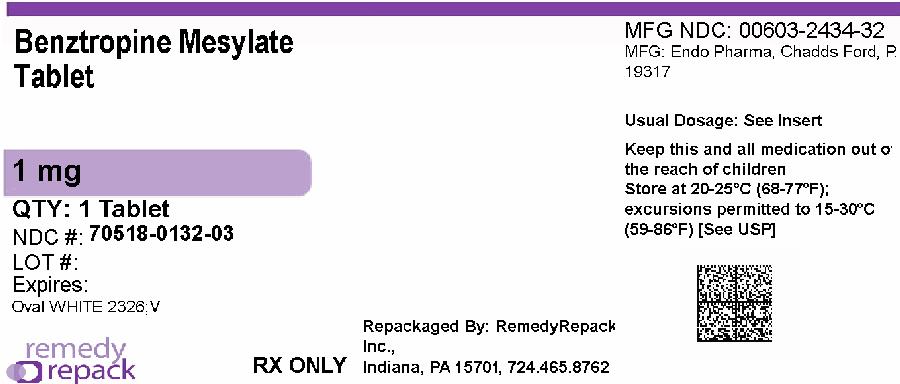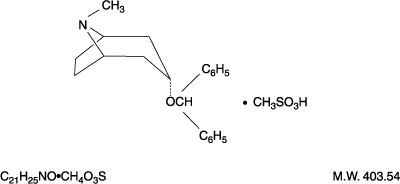 DRUG LABEL: Benztropine Mesylate
NDC: 70518-0132 | Form: TABLET
Manufacturer: REMEDYREPACK INC.
Category: prescription | Type: HUMAN PRESCRIPTION DRUG LABEL
Date: 20260218

ACTIVE INGREDIENTS: BENZTROPINE MESYLATE 1 mg/1 1
INACTIVE INGREDIENTS: CALCIUM PHOSPHATE, DIBASIC, DIHYDRATE; CROSCARMELLOSE SODIUM; LACTOSE MONOHYDRATE; MAGNESIUM STEARATE; CELLULOSE, MICROCRYSTALLINE

BENZTROPINE MESYLATE TABLETS, USP 0.5 mg, 1 mg and 2 mg

Rx only

DESCRIPTION

Benztropine mesylate is a synthetic compound containing structural features found in atropine and diphenhydramine.

It is a crystalline white powder, very soluble in water, designated as 3α-(Diphenylmethoxy)-1αH, 5αH-tropane methanesulfonate, with the following structural formula:

Each tablet, for oral administration, contains 0.5 mg, 1 mg or 2 mg of benztropine mesylate.

Each tablet contains the following inactive ingredients: croscarmellose sodium, dibasic calcium phosphate, lactose monohydrate, magnesium stearate and microcrystalline cellulose.

CLINICAL PHARMACOLOGY

Benztropine mesylate possesses both anticholinergic and antihistaminic effects, although only the former have been established as therapeutically significant in the management of parkinsonism.

In the isolated guinea pig ileum, the anticholinergic activity of this drug is about equal to that of atropine; however, when administered orally to unanesthetized cats, it is only about half as active as atropine.

In laboratory animals, its antihistaminic activity and duration of action approach those of pyrilamine maleate.

INDICATIONS AND USAGE

For use as an adjunct in the therapy of all forms of parkinsonism.

Useful also in the control of extrapyramidal disorders (except tardive dyskinesia – see PRECAUTIONS) due to neuroleptic drugs (e.g., phenothiazines).

CONTRAINDICATIONS

Hypersensitivity to benztropine mesylate tablets.

Because of its atropine-like side effects, this drug is contraindicated in pediatric patients under three years of age, and should be used with caution in older pediatric patients.

WARNINGS

Safe use in pregnancy has not been established.

Benztropine mesylate may impair mental and/or physical abilities required for performance of hazardous tasks, such as operating machinery or driving a motor vehicle.

When benztropine mesylate is given concomitantly with phenothiazines, haloperidol, or other drugs with anticholinergic or antidopaminergic activity, patients should be advised to report gastrointestinal complaints, fever or heat intolerance promptly. Paralytic ileus, hyperthermia and heat stroke, all of which have sometimes been fatal, have occurred in patients taking anticholinergic-type antiparkinsonism drugs, including benztropine mesylate, in combination with phenothiazines and/or tricyclic antidepressants.

Since benztropine mesylate contains structural features of atropine, it may produce anhidrosis. For this reason, it should be administered with caution during hot weather, especially when given concomitantly with other atropine-like drugs to the chronically ill, the alcoholic, those who have central nervous system disease, and those who do manual labor in a hot environment. Anhidrosis may occur more readily when some disturbance of sweating already exists. If there is evidence of anhidrosis, the possibility of hyperthermia should be considered. Dosage should be decreased at the discretion of the physician so that the ability to maintain body heat equilibrium by perspiration is not impaired. Severe anhidrosis and fatal hyperthermia have occurred.

PRECAUTIONS

General

Since benztropine mesylate has cumulative action, continued supervision is advisable. Patients with a tendency to tachycardia and patients with prostatic hypertrophy should be observed closely during treatment.

Dysuria may occur, but rarely becomes a problem. Urinary retention has been reported with benztropine mesylate.

The drug may cause complaints of weakness and inability to move particular muscle groups, especially in large doses. For example, if the neck has been rigid and suddenly relaxes, it may feel weak, causing some concern. In this event, dosage adjustment is required.

Mental confusion and excitement may occur with large doses, or in susceptible patients. Visual hallucinations have been reported occasionally. Furthermore, in the treatment of extrapyramidal disorders due to neuroleptic drugs (e.g., phenothiazines), in patients with mental disorders, occasionally there may be intensification of mental symptoms. In such cases, antiparkinsonian drugs can precipitate a toxic psychosis. Patients with mental disorders should be kept under careful observation, especially at the beginning of treatment or if dosage is increased.

Tardive dyskinesia may appear in some patients on long-term therapy with phenothiazines and related agents, or may occur after therapy with these drugs has been discontinued. Antiparkinsonism agents do not alleviate the symptoms of tardive dyskinesia, and in some instances may aggravate them. Benztropine mesylate is not recommended for use in patients with tardive dyskinesia.

The physician should be aware of the possible occurrence of glaucoma. Although the drug does not appear to have any adverse effect on simple glaucoma, it probably should not be used in angle-closure glaucoma.

Drug Interactions

Antipsychotic drugs such as phenothiazines or haloperidol; tricyclic antidepressants (see WARNINGS).

Pediatric Use

Because of the atropine-like side effects, benztropine mesylate should be used with caution in pediatric patients over three years of age (see CONTRAINDICATIONS).

ADVERSE REACTIONS

The adverse reactions below, most of which are anticholinergic in nature, have been reported and within each category are listed in order of decreasing severity.

Cardiovascular Tachycardia.

Digestive Paralytic ileus, constipation, vomiting, nausea, dry mouth.

If dry mouth is so severe that there is difficulty in swallowing or speaking, or loss of appetite and weight, reduce dosage or discontinue the drug temporarily.

Slight reduction in dosage may control nausea and still give sufficient relief of symptoms. Vomiting may be controlled by temporary discontinuation, followed by resumption at a lower dosage.

Nervous System Toxic psychosis, including confusion, disorientation, memory impairment, visual hallucinations; exacerbation of pre-existing psychotic symptoms; nervousness; depression; listlessness; numbness of fingers.

Special Senses Blurred vision, dilated pupils.

Urogenital Urinary retention, dysuria.

Metabolic/Immune or Skin Occasionally, an allergic reaction, e.g., skin rash, develops. If this cannot be controlled by dosage reduction, the medication should be discontinued.

Other Heat stroke, hyperthermia, fever.

OVERDOSAGE

Manifestations

May be any of those seen in atropine poisoning or antihistamine overdosage; CNS depression, preceded or followed by stimulation; confusion; nervousness; listlessness; intensification of mental symptoms or toxic psychosis in patients with mental illness being treated with neuroleptic drugs (e.g., phenothiazines); hallucinations (especially visual); dizziness; muscle weakness; ataxia; dry mouth; mydriasis, blurred vision; palpitations; tachycardia; elevated blood pressure; nausea; vomiting; dysuria; numbness of fingers; dysphagia; allergic reactions, e.g., skin rash; headache; hot, dry, flushed skin; delirium; coma; shock; convulsions; respiratory arrest; anhidrosis; hyperthermia; glaucoma; constipation.

Treatment

Physostigmine salicylate, 1 to 2 mg, SC or IV, reportedly will reverse symptoms of anticholinergic intoxication. * A second injection may be given after 2 hours if required. Otherwise treatment is symptomatic and supportive. Induce emesis or perform gastric lavage (contraindicated in precomatose convulsive, or psychotic states). Maintain respiration. A short-acting barbiturate may be used for CNS excitement, but with caution to avoid subsequent depression; supportive care for depression (avoid convulsant stimulants such as picrotoxin, pentylenetetrazol, or bemegride); artificial respiration for severe respiratory depression; a local miotic for mydriasis and cycloplegia; ice bags or other cold applications and alcohol sponges for hyperpyrexia, a vasopressor and fluids for circulatory collapse. Darken room for photophobia.

DOSAGE AND ADMINISTRATION

Benztropine mesylate tablets should be used when patients are able to take oral medication.

Because of cumulative action, therapy should be initiated with a low dose which is increased gradually at five- or six-day intervals to the smallest amount necessary for optimal relief. Increases should be made in increments of 0.5 mg, to a maximum of 6 mg, or until optimal results are obtained without excessive adverse reactions.

Postencephalitic and Idiopathic Parkinsonism

The usual daily dose is 1 to 2 mg with a range of 0.5 to 6 mg orally.

As with any agent used in parkinsonism, dosage must be individualized according to age and weight, and the type of parkinsonism being treated. Generally, older patients, and thin patients cannot tolerate large doses. Most patients with postencephalitic parkinsonism need fairly large doses and tolerate them well. Patients with a poor mental outlook are usually poor candidates for therapy.

In idiopathic parkinsonism, therapy may be initiated with a single daily dose of 0.5 to 1 mg at bedtime. In some patients, this will be adequate; in others 4 to 6 mg a day may be required.

In postencephalitic parkinsonism, therapy may be initiated in most patients with 2 mg a day in one or more doses. In highly sensitive patients, therapy may be initiated with 0.5 mg at bedtime, and increased as necessary.

Some patients experience greatest relief by taking the entire dose at bedtime; others react more favorably to divided doses, two to four times a day. Frequently, one dose a day is sufficient, and divided doses may be unnecessary or undesirable.

The long duration of action of this drug makes it particularly suitable for bedtime medication when its effects may last throughout the night, enabling patients to turn in bed during the night more easily, and to rise in the morning.

When benztropine mesylate is started, do not terminate therapy with other antiparkinsonian agents abruptly. If the other agents are to be reduced or discontinued, it must be done gradually. Many patients obtain greatest relief with combination therapy.

Benztropine mesylate may be used concomitantly with carbidopa-levodopa, or with levodopa, in which case periodic dosage adjustment may be required in order to maintain optimum response.

Drug-Induced Extrapyramidal Disorders

In treating extrapyramidal disorders due to neuroleptic drugs (e.g., phenothiazines), the recommended dosage is 1 to 4 mg once or twice a day orally. Dosage must be individualized according to the need of the patient. Some patients require more than recommended; others do not need as much.

When extrapyramidal disorders develop soon after initiation of treatment with neuroleptic drugs (e.g., phenothiazines), they are likely to be transient. One to 2 mg of benztropine mesylate tablets two or three times a day usually provides relief within one or two days. After one or two weeks the drug should be withdrawn to determine the continued need for it. If such disorders recur, benztropine mesylate can be reinstituted.

Certain drug-induced extrapyramidal disorders that develop slowly may not respond to benztropine mesylate.

HOW SUPPLIED

Benztropine Mesylate Tablets, USP are available as follows:

1 mg: white, oval, scored tablets, debossed "2326" on one side and debossed "V" on the reverse side, supplied in

NDC: 70518-0132-00

NDC: 70518-0132-01

NDC: 70518-0132-02

NDC: 70518-0132-03

PACKAGING: 30 in 1 BLISTER PACK

PACKAGING: 30 in 1 BLISTER PACK

PACKAGING: 100 in 1 BOX

PACKAGING: 1 in 1 POUCH

Dispense in a well-closed container as defined in the USP.

Store at 20° to 25°C (68° to 77°F) [see USP Controlled Room Temperature].

Repackaged and Distributed By:

Remedy Repack, Inc.

625 Kolter Dr. Suite #4 Indiana, PA 1-724-465-8762

Repackaged and Distributed By:

Remedy Repack, Inc.

625 Kolter Dr. Suite #4 Indiana, PA 1-724-465-8762

PRINCIPAL DISPLAY PANEL

DRUG: Benztropine Mesylate

GENERIC: benztropine mesylate

DOSAGE: TABLET

ADMINSTRATION: ORAL

NDC: 70518-0132-0

NDC: 70518-0132-1

NDC: 70518-0132-2

NDC: 70518-0132-3

COLOR: white

SHAPE: OVAL

SCORE: Two even pieces

SIZE: 10 mm

IMPRINT: 2326;V

PACKAGING: 30 in 1 BLISTER PACK

PACKAGING: 30 in 1 BLISTER PACK

OUTER PACKAGING: 100 in 1 BOX

PACKAGING: 1 in 1 POUCH

ACTIVE INGREDIENT(S):

- BENZTROPINE MESYLATE 1mg in 1

INACTIVE INGREDIENT(S):

- CROSCARMELLOSE SODIUM
- CALCIUM PHOSPHATE, DIBASIC, DIHYDRATE
- LACTOSE MONOHYDRATE
- MAGNESIUM STEARATE
- CELLULOSE, MICROCRYSTALLINE